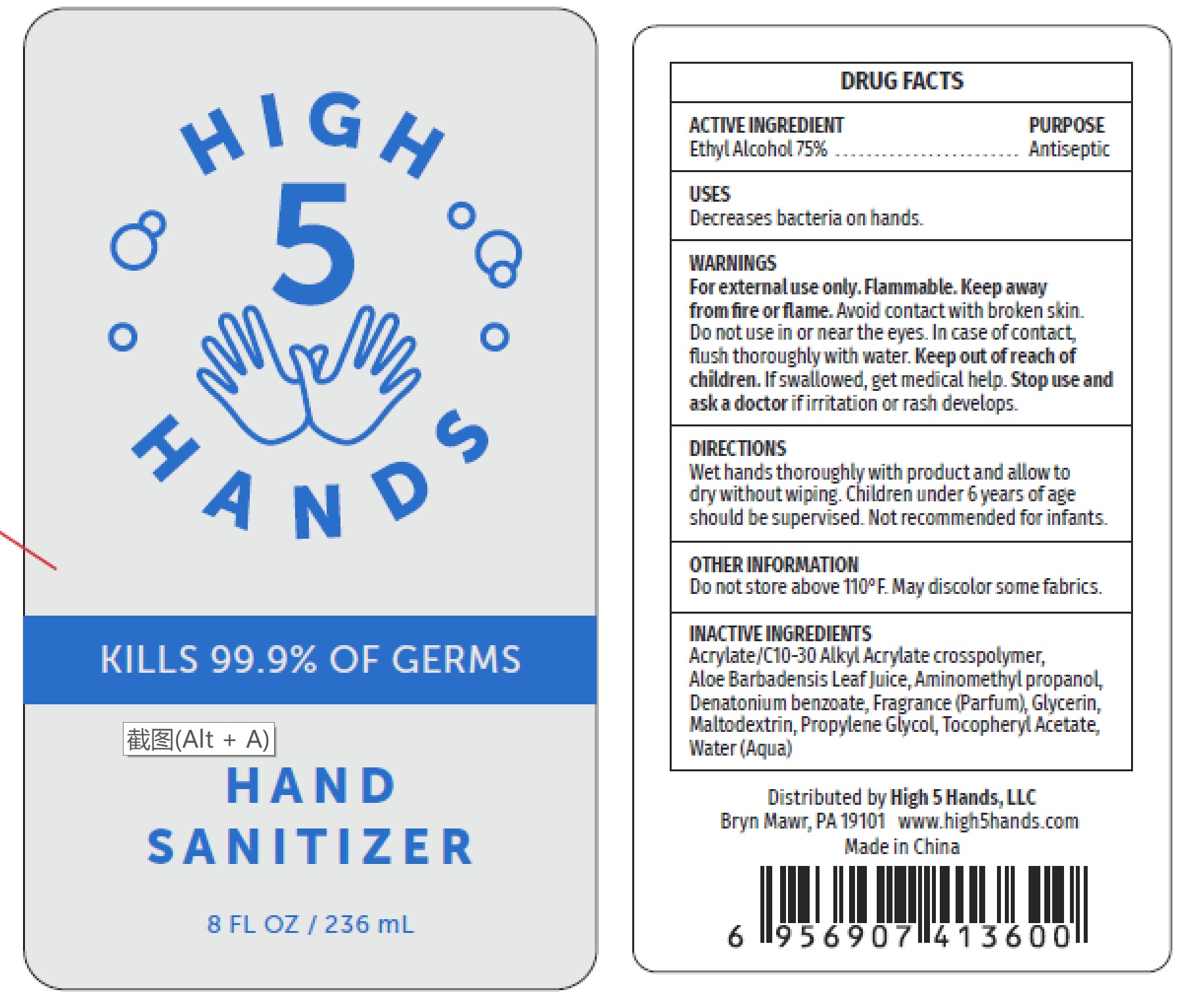 DRUG LABEL: Hand Sanitizer
NDC: 78869-008 | Form: GEL
Manufacturer: HIGH 5 HANDS LLC
Category: otc | Type: HUMAN OTC DRUG LABEL
Date: 20200610

ACTIVE INGREDIENTS: ALCOHOL 75 mL/100 mL
INACTIVE INGREDIENTS: MALTODEXTRIN; PROPYLENE GLYCOL; WATER; ALOE VERA LEAF; GLYCERIN; CARBOMER INTERPOLYMER TYPE A (55000 CPS); .ALPHA.-TOCOPHEROL ACETATE; AMINOMETHYLPROPANOL; DENATONIUM BENZOATE

ACTIVE INGREDIENT

Ethyl Alcohol 75%

Purpose
Antiseptic

USES

Decreases bacteria on hands.

WARNINGS

For external use only. Flammable. Keep away

from fire or flame. Avoid contact with broken skin.

Do not use in or near the eyes. In case of contact, flush thoroughly with water.

Stop use and ask a doctor if irritation or rash develops.

Keep out of reach of children. If swallowed, get medical help.

DIRECTIONS

Wet hands thoroughly with product and allow to dry without wiping. Children under 6 years of age should be supervised. Not recommended for infants.

OTHER INFORMATION

Do not store above 110°F. May discolor some fabrics.

INACTIVE INGREDIENTS

Acrylate/C10-30 Alkyl Acrylate crosspolymer, Aloe Barbadensis Leaf Juice, Aminomethyl propanol,

Denatonium benzoate, Fragrance (Parfum), Glycerin, Maltodextrin, Propylene Glycol, Tocopheryl Acetate, Water (Aqua)